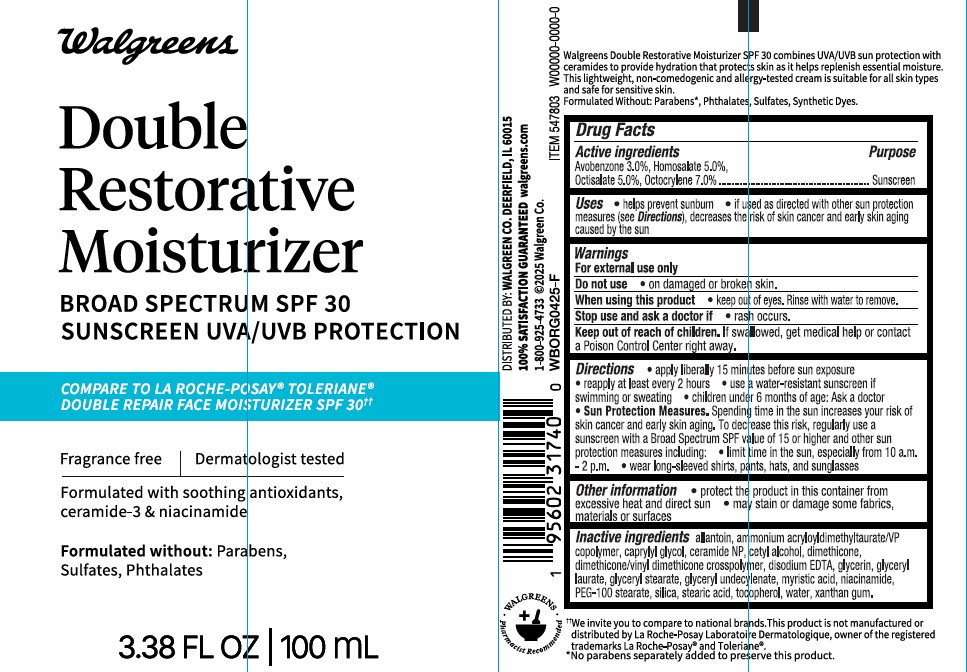 DRUG LABEL: Walgreens Double Restorative Moisturizer Broad Spectrum SPF 30 Sunscreen
NDC: 0363-0435 | Form: LOTION
Manufacturer: WALGREEN COMPANY
Category: otc | Type: HUMAN OTC DRUG LABEL
Date: 20250624

ACTIVE INGREDIENTS: HOMOSALATE 50 mg/1 mL; OCTISALATE 50 mg/1 mL; OCTOCRYLENE 70 mg/1 mL; AVOBENZONE 30 mg/1 mL
INACTIVE INGREDIENTS: CERAMIDE NP; DIMETHICONE/VINYL DIMETHICONE CROSSPOLYMER (SOFT PARTICLE); GLYCERYL LAURATE; STEARIC ACID; GLYCERYL 1-UNDECYLENATE; .ALPHA.-TOCOPHEROL, DL-; ALLANTOIN; NIACINAMIDE; PEG-100 STEARATE; AMMONIUM ACRYLOYLDIMETHYLTAURATE/VP COPOLYMER; CETYL ALCOHOL; GLYCERYL STEARATE; SILICON DIOXIDE; WATER; GLYCERIN; EDETATE DISODIUM ANHYDROUS; CAPRYLYL GLYCOL; DIMETHICONE; XANTHAN GUM

Walgreens Double Restorative Moisturizer Broad Spectrum SPF 30 Sunscreen

Active ingredients

Avobenzone 3.0%, Homosalate 5.0%, Octisalate 5.0%, Octocrylene 7.0%

Purpose

Sunscreen

Uses

- helps prevent sunburn
- if used as directed with other sun protection measures (see Directions), decreases the risk of skin cancer and early aging caused by the sun

Warnings

For external use only

Do not use on

• on damaged or broken skin

When using this product

• keep out of eyes. Rinse with water to remove.

Stop use and ask a doctor if

• rash occurs

Keep out of reach of children.

If swallowed, get medical help or contact a Poison Control Center right away.

Directions

- apply liberally 15 minutes before sun exposure
- Reapply:
- after 80 minutes of swimming or sweating
- immediately after towel drying
- at least every 2 hours
- children under 6 months of age: Ask a doctor
- Sun Protection Measures. Spending time in the sun increases your risk of skin cancer and early skin aging. To decrease this risk, regularly use a sunscreen with a Broad Spectrum SPF value of 15 or higher and other sun protection measures including:
- limit time in the sun especially from 10 a.m. – 2 p.m.
- wear long-sleeved shirts, pants, hats, and sunglasses

Other Information

- protect the product in this container from excessive heat and direct sun
- may stain or damage some fabrics, materials or surfaces

Inactive ingredients

allantoin, ammonium acryloyldimethyltaurate/VP copolymer, caprylyl glycol, ceramide NP, cetyl alcohol, dimethicone, dimethicone/vinyl dimethicone crosspolymer, disodium EDTA, glycerin, glyceryl laurate, glyceryl stearate, glyceryl undecylenate, myristic acid, niacinamide, PEG-100 stearate, silica, stearic acid, tocopherol, water, xanthan gum.